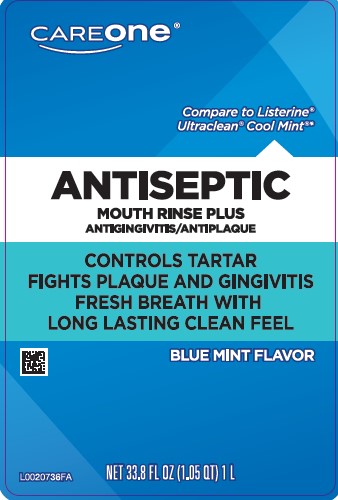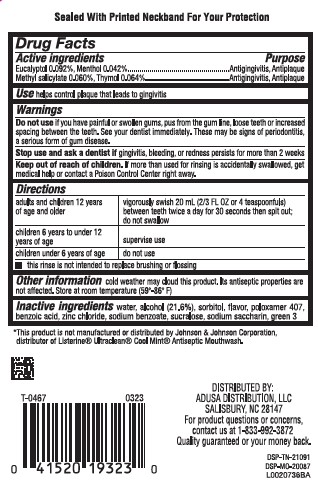 DRUG LABEL: Tartar control plus
NDC: 72476-558 | Form: MOUTHWASH
Manufacturer: Retail Business Services, LLC 
Category: otc | Type: HUMAN OTC DRUG LABEL
Date: 20260206

ACTIVE INGREDIENTS: EUCALYPTOL 0.92 mg/1 mL; MENTHOL 0.42 mg/1 mL; METHYL SALICYLATE 0.6 mg/1 mL; THYMOL 0.64 mg/1 mL
INACTIVE INGREDIENTS: WATER; ALCOHOL; SORBITOL; POLOXAMER 407; BENZOIC ACID; ZINC CHLORIDE; SODIUM BENZOATE; SUCRALOSE; SACCHARIN SODIUM; FD&C GREEN NO. 3

Care One 855.000/855AA-AC
Tartar Control Plus Antiseptic Mouth Rinse, Blue Mint

TEP

Sealed With Printed Neckband For Your Protection

Active ingredients

Eucalyptol 0.092%

Menthol 0.042%

Methyl salicylate 0.060%

Thymol 0.064%

Purpose

Antigingivitis, Antiplaque

Use

helps control plaque that leads to gingivitis

Warnings

For this product

Do not use

if you have painful or swollen gums, pus from the gum line, loose teeth or increased spacing between the teeth. See your dentist immediately. These may be signs of periodontitis, a serious form of gum disease.

Stop use and ask a dentist if

gingivitis, bleeding, or redness persists for more than 2 weeks.

Keep out of reach of children.

If more than used for rinsing is accidentally swallowed, get medical help or contact a Poison Control Center right away.

Directions

adults and children 12 years of age and older - vigorously swish 20 mL (2/3 FL OZ or 4 teaspoonfuls) between teeth for 30 seconds then spit out; do not swallow

children 6 years to under 12 years of age - supervise use

children under 6 years of age - do not use

- this rinse is not intended to replace brushing or flossing

Other information

cold weather may cloud this product. Its antiseptic properties are not affected. Store at room temperature (59°-86°F)

Inactive ingredients

water, alcohol 21.6%, sorbitol, flavor, poloxamer 407, benzoic acid, zinc chloride, sodium benzoate, sucralose, sodium saccharin, green 3

ADVERSE REACTION

*This product is not manufactured or distributed by Johnson & Johnson Corportation, distributor of Listerine Ultraclean Coll Mint Antiseptic Mouthwash

DISTRIBUTED BY:

ADUSA DISTRIBUTION, LLC

SALISBURY, NC 28147

For product questions or concerns,

contract us at 1-833-992-3872

Quality guaranteed or your money back.

DSP-TN-21091

DSP-MO-20087

Principal display panel

CAREONE

Compare to Listerine UltracleanCool Mint*

ANTISEPTIC

MOUTH RINSE PLUS

ANTIGINGIVITIS/ANTIPLAQUE

CONTROLS TARTAR

FIGHTS PLAQUE AND GINGIVITIS

FRESH BREATH WITH LONG LASTING CLEAN FEEL

BLUE MINT FLAVOR

NET 33.8 FL OZ (1.05 QT) 1 L